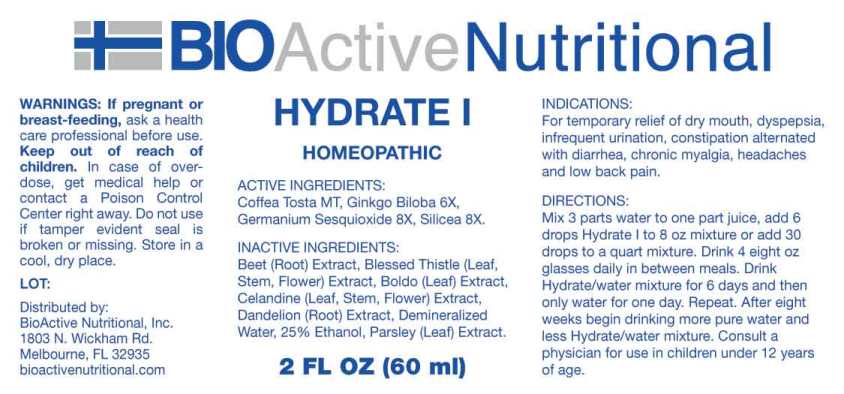 DRUG LABEL: Hydrate
NDC: 43857-0198 | Form: LIQUID
Manufacturer: BioActive Nutritional, Inc.
Category: homeopathic | Type: HUMAN OTC DRUG LABEL
Date: 20241017

ACTIVE INGREDIENTS: COFFEA ARABICA SEED, ROASTED 1 [hp_X]/1 mL; GINKGO 6 [hp_X]/1 mL; GERMANIUM SESQUIOXIDE 8 [hp_X]/1 mL; SILICON DIOXIDE 8 [hp_X]/1 mL
INACTIVE INGREDIENTS: CHELIDONIUM MAJUS; BETA VULGARIS; CENTAUREA BENEDICTA FLOWERING TOP; PEUMUS BOLDUS LEAF; TARAXACUM OFFICINALE ROOT; PARSLEY; WATER; ALCOHOL

DRUG FACTS:

ACTIVE INGREDIENTS:

Coffea Tosta 1X, Ginkgo Biloba 6X, Germanium Sesquioxide 8X, Silica 8X.

INDICATIONS:

For temporary relief of dry mouth, dyspepsia, infrequent urination, constipation alternated with diarrhea, chronic myalgia, headaches and low back pain.

WARNINGS:

If pregnant or breast-feeding, ask a health care professional before use.

Keep out of reach of children. In case of overdose, get medical help or contact a Poison Control Center right away.

Do not use if tamper evident seal is broken or missing.

Store in a cool, dry place.

Keep out of reach of children. In case of overdose, get medical help or contact Poison Control Center right away.

DIRECTIONS:

Mix 3 parts water to one part juice, add 6 drops Hydrate I to 8 oz mixture or add 30 drops to a quart mixture. Drink 4 eight oz glasses daily in between meals. Drink Hydrate/water mixture for 6 days and then only water for one day. Repeat. After eight weeks begin drinking more pure water and less Hydrate/water mixture. Consult a physician for use in children under 12 years of age.

INDICATIONS:

For temporary relief of dry mouth, dyspepsia, infrequent urination, constipation alternated with diarrhea, chronic myalgia, headaches and low back pain.

INACTIVE INGREDIENTS:

Celandine (Leaf, Stem, Flower) Chelidonium Majus, Beet (Root) Beta Vulgaris, Blessed Thistle (Leaf, Stem, Flower) Cnicus Benedictus, Boldo (Leaf) Peumus Boldus, Dandelion (Root) Taraxacum Officinale, Parsley (Leaf) Petroselinum Crispum, Demineralized Water, 25% Ethanol.

QUESTIONS:

Distributed by:
BioActive Nutritional, Inc.
1803 N. Wickham Rd.
Melbourne, FL 32935
bioactivenutritional.com

PACKAGE LABEL DISPLAY:

BIOActive Nutritional

HYDRATE I

HOMEOPATHIC

2 FL OZ (60 ml)